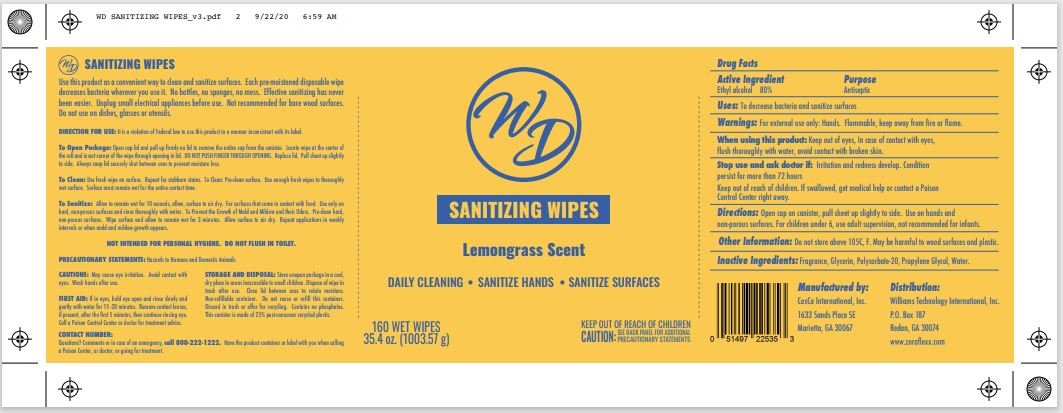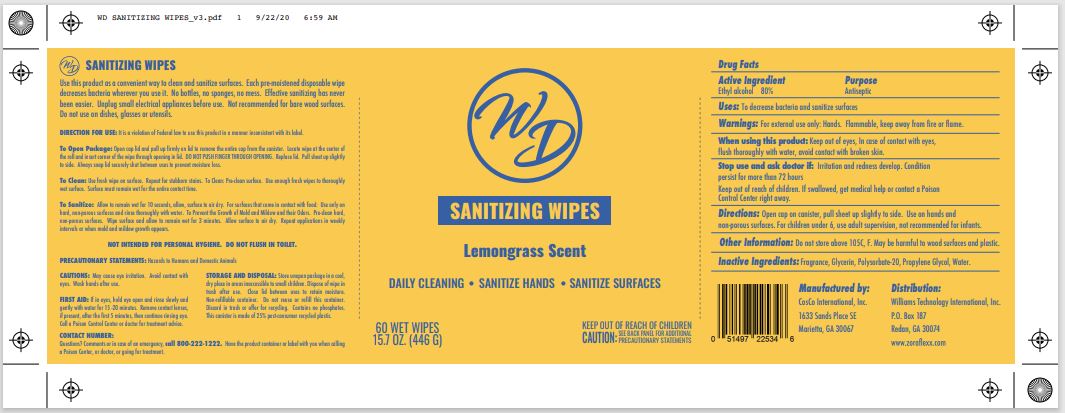 DRUG LABEL: WD Sanitizing Wipes Lemongrass Scent
NDC: 77515-0008 | Form: CLOTH
Manufacturer: Williams Technology International, Inc
Category: otc | Type: HUMAN OTC DRUG LABEL
Date: 20201001

ACTIVE INGREDIENTS: ALCOHOL .80 1/1 1
INACTIVE INGREDIENTS: GLYCERIN; POLYSORBATE 20; PROPYLENE GLYCOL; WATER

Active Ingredient(s)

Alcohol 80% v/v. Purpose: Antiseptic

Purpose

Antiseptic

Uses:

To decrease bacteria and sanitize surfaces

Warnings:

For external use only: Hands. Flammable. Keep away from fire or flame.

When using this product keep out of eyes. In case of contact with eyes, rinse thoroughly with water, avoid contact with broken skin.

Stop use and ask a doctor if irritation and redness develop. Condition persist for more than 72 hours.

Keep out of reach of children. If swallowed, get medical help or contact a Poison Control Center right away.

Directions:

Open cap on canister, pull sheet up slightly to side. Use on hands and non-porous surfaces. For children under 6, use adult supervision, not recommended for infants.

Other Information:

Do not store above 105F. May be harmful to wood surfaces and plastic.

Inactive ingredients:

Fragrance, Glycerin, Polysorbate-20, Propylene Glycol, Water